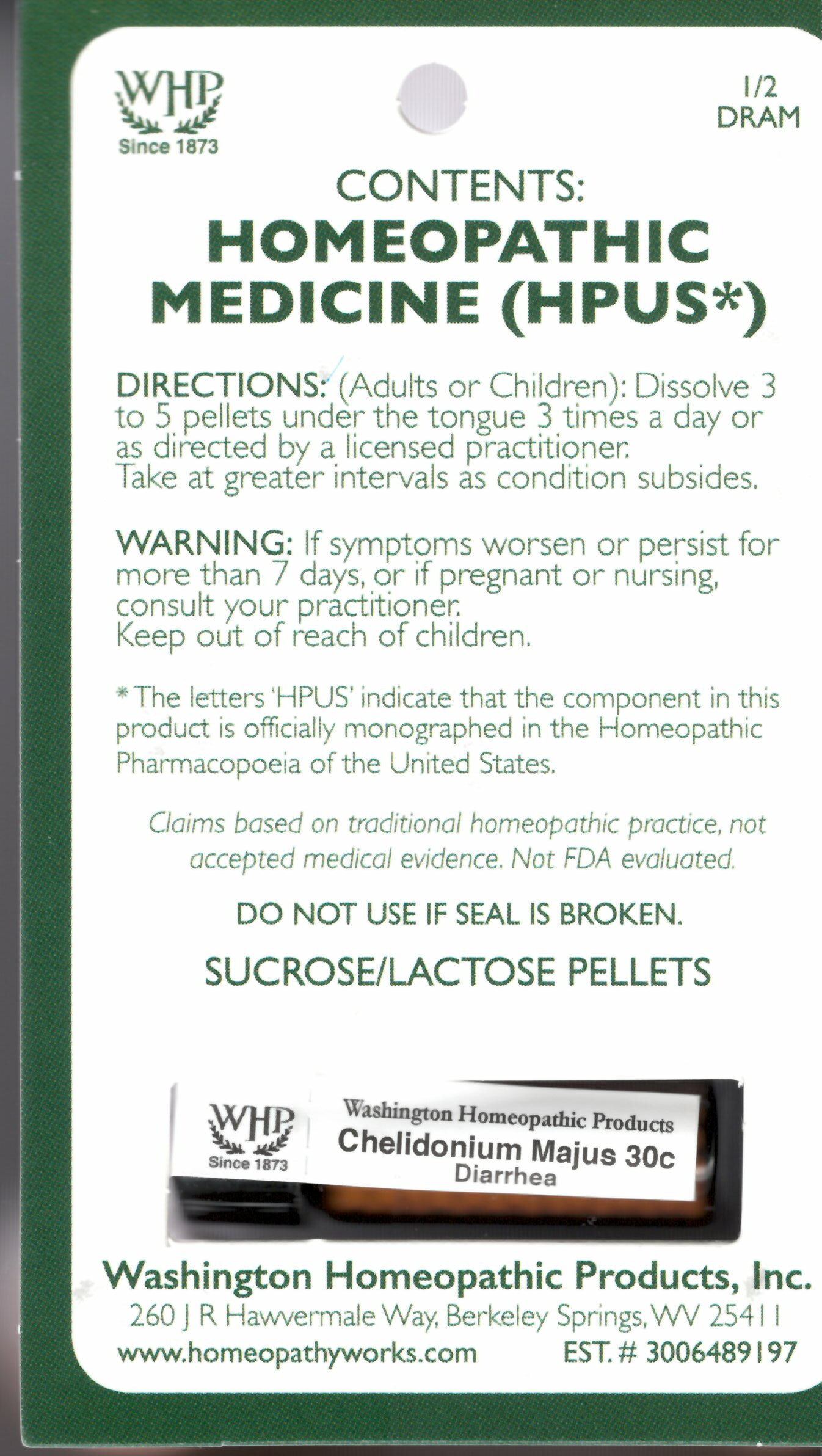 DRUG LABEL: Chelidonium majus
NDC: 71919-816 | Form: PELLET
Manufacturer: Washington Homeopathic Products
Category: homeopathic | Type: HUMAN OTC DRUG LABEL
Date: 20250128

ACTIVE INGREDIENTS: CHELIDONIUM MAJUS 30 [hp_C]/1 1
INACTIVE INGREDIENTS: LACTOSE; SUCROSE

Chelidonium majus Kit Refill 30c

ACTIVE INGREDIENTS

Chelidonium majus 30c

USES

Indicated for Diarrhea.

KEEP OUT OF REACH OF CHILDREN

As with all medications, keep out of reach of children.

INDICATIONS

CHELIDONIUM MAJ Indicated for Diarrhea

STOP USE AND ASK DOCTOR

If symptoms persist or recur, discontinue use. If pregnant or nursing, consult a licensed practitioner before using this product

DIRECTIONS

(Adults or Children): Dissolve 3 to 5 pellets under tongue 3 times a day or as directed by a licensed practitioner. Take at greater intervals as condition subsides.

INACTIVE INGREDIENTS

Sucrose/Lactose